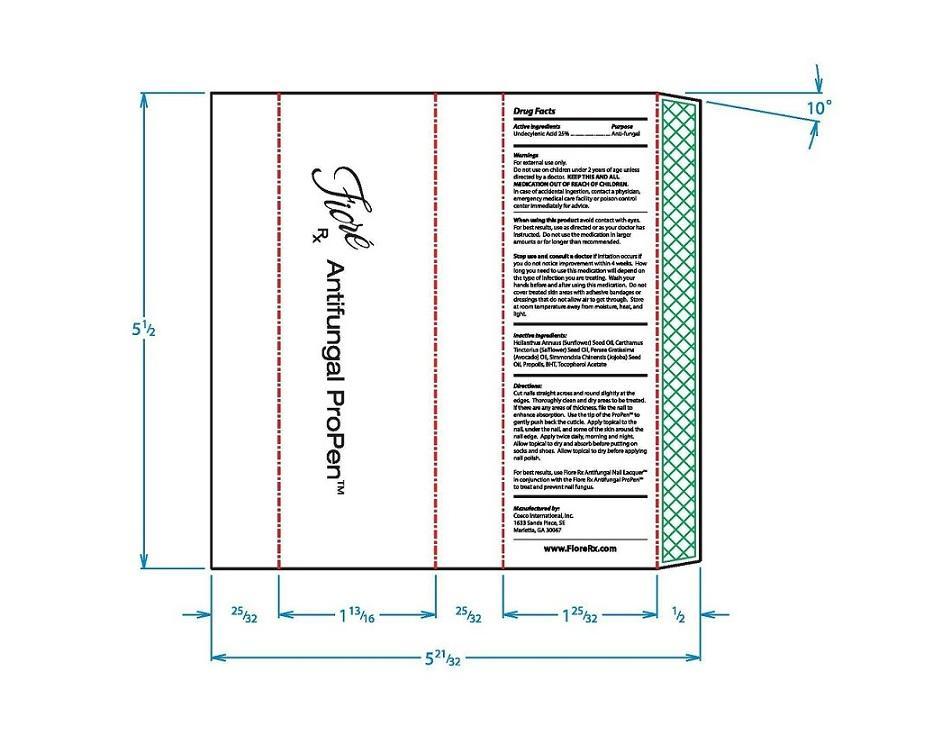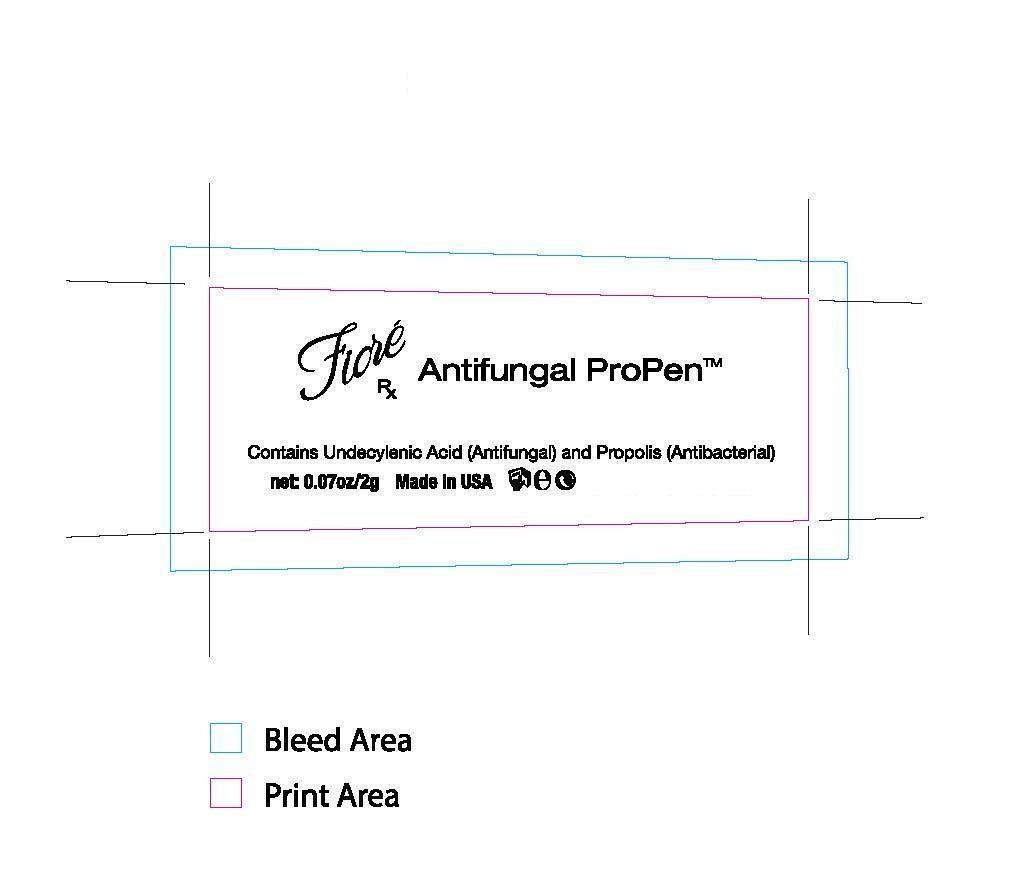 DRUG LABEL: Fiore Rx Antifungal ProPen
NDC: 52261-2500 | Form: LIQUID
Manufacturer: Cosco International, Inc.
Category: otc | Type: HUMAN OTC DRUG LABEL
Date: 20130919

ACTIVE INGREDIENTS: Undecylenic Acid 0.5 g/2 g
INACTIVE INGREDIENTS: SUNFLOWER SEED 1.4368 g/2 g; SAFFLOWER OIL 0.03 g/2 g; AVOCADO OIL 0.02 g/2 g; SIMMONDSIA CHINENSIS SEED 0.01 g/2 g; PROPOLIS WAX 0.002 g/2 g; BUTYLATED HYDROXYTOLUENE 0.001 g/2 g; .ALPHA.-TOCOPHEROL ACETATE 0.0002 g/2 g

Drug Facts

Active Ingredient Purpose
Undecylenic Acid 3%........................Anti-fungal

PURPOSE

Anti-fungal

Warnings For external use only.

Do not use on children under 2 years of age unless directed by a doctor.
KEEP THIS AND ALL MEDICATION OUT OF REACH OF CHILDREN.In case of accidental ingestion, contact a physician, emergency medical care facility or poison control center immediately for advice.

When using this product avoid contact with eyes.

Stop use and ask a doctor if irritation occurs.

Directions:

Cut nail straight across and round slightly at the edges. Throughly clean and dry areas to be treated. If there are any ares of thickness, file the nail to enhance absorption. Use the tip of the ProPen™ to gently push back the cuticle. Apply topical to the nail, under the nail, and some of the skin around the nail edge. Apply twice daily, morning and night. Allow topical to dry and absorb before putting on socks and shoes. Allow topical to dry before applying nail polish.

For best results, use Fiore Rx Antifungal Nail Lacquer™ in conjuction with the Fiore Rx Antifungal ProPen™ to treat and prevent nail fungus.

Inactive ingredients:

Helianthus Annuus (Sunflower) Seed Oil, Carthamus Tinctorius (Safflower) Seed Oil, Persea Gratissima (Avacado) Oil, Simmondsia Chinensis (Jojoba) Seed Oil, Propolis Wax, BHT, Tocopheral Acetate